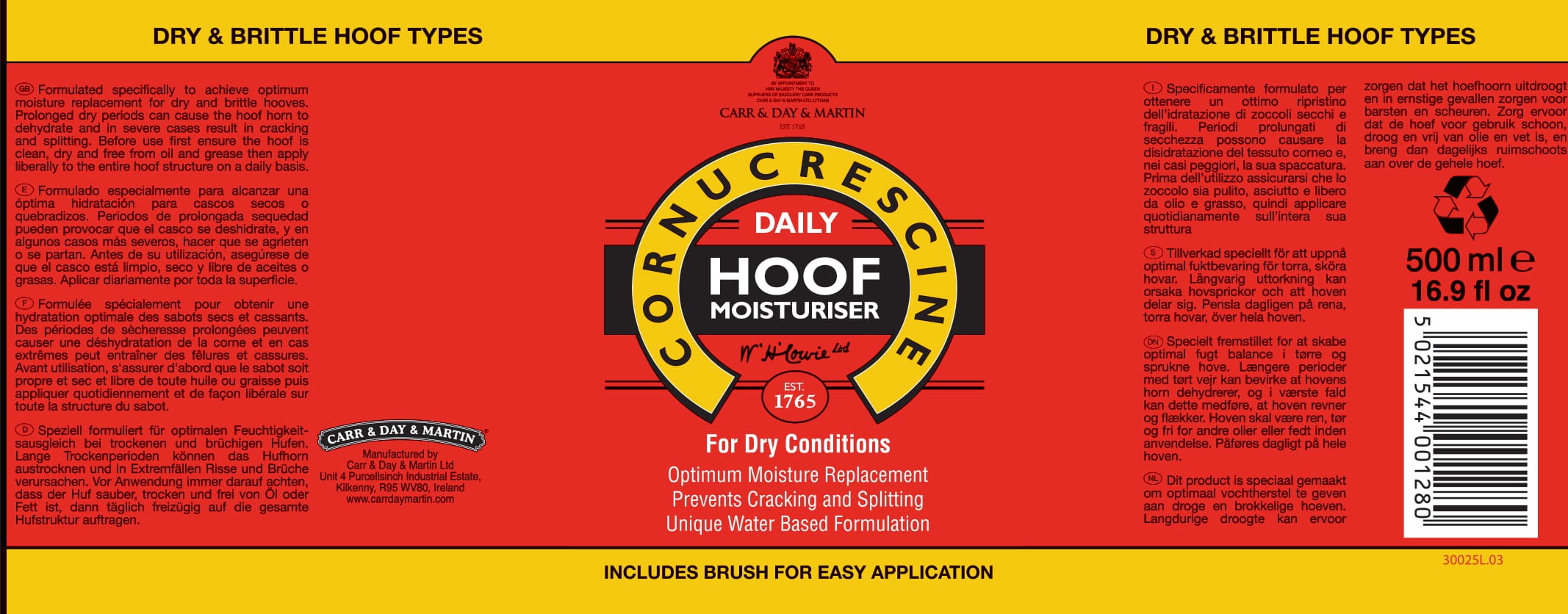 DRUG LABEL: Cornucrescine Daily Hoof Moisturiser
NDC: 43258-325 | Form: EMULSION
Manufacturer: Carr & Day & Martin Unlimited Company
Category: animal | Type: OTC ANIMAL DRUG LABEL
Date: 20250107

ACTIVE INGREDIENTS: Glycerin 100 g/1 L; .ALPHA.-TOCOPHEROL .5 g/1 L; CETOSTEARYL ALCOHOL 32.6 g/1 L

INDICATIONS AND USAGE

Formulated specifically to achieve optimum moisture replacement for dry and brittle hooves. Prolonged dry periods can cause the hoof horn to dehydrate and in severe cases result in cracking and splitting.

DOSAGE AND ADMINISTRATION

Before use first ensure the hoof is clean, dry and fee from oil and grease then apply liberally to the entire hoof structure on a daily basis.

Manaufactured by

Carr & Day & Martin Unlimited Company

Unit 4 Purcellsinch Industrial Estate,

Kilkenny, R95 WV80, Ireland

www.carrdaymartin.com